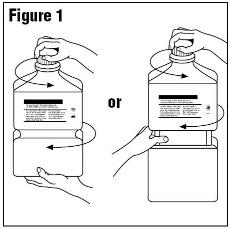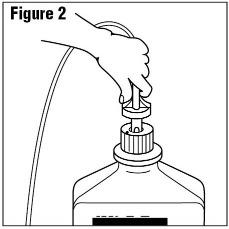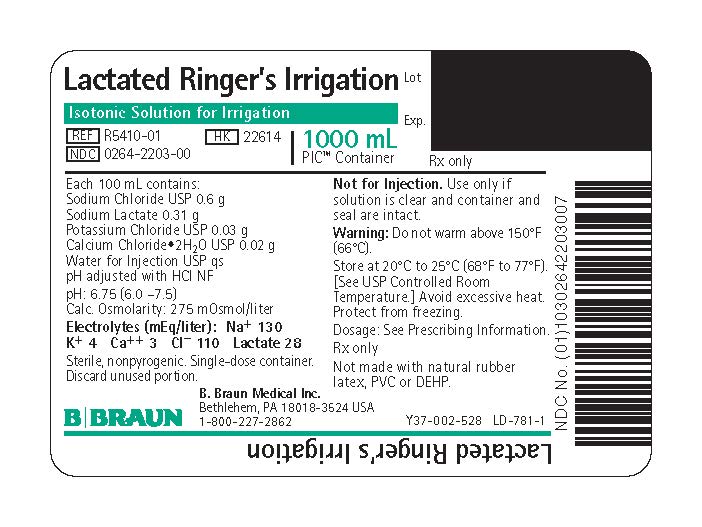 DRUG LABEL: Lactated Ringers
NDC: 0264-2203 | Form: IRRIGANT
Manufacturer: B. Braun Medical Inc.
Category: prescription | Type: HUMAN PRESCRIPTION DRUG LABEL
Date: 20230907

ACTIVE INGREDIENTS: SODIUM CHLORIDE 0.6 g/100 mL; SODIUM LACTATE 0.31 g/100 mL; POTASSIUM CHLORIDE 0.03 g/100 mL; CALCIUM CHLORIDE 0.02 g/100 mL
INACTIVE INGREDIENTS: WATER

Lactated Ringer's Irrigation

Y36-002-965 LD-780-1

Package Insert

PIC™ (Plastic Irrigation Container)

FOR ALL GENERAL IRRIGATION, WASHING AND RINSING PURPOSES

Not For Injection By Usual Parenteral•Routes

Semi-rigid Irrigation Container

Isotonic Solution for Irrigation.

For Irrigation Only. Not for Injection.

Rx only

DESCRIPTION

Lactated Ringer's Irrigation is a sterile, nonpyrogenic, solution of electrolytes in water for injection intended only for sterile irrigation, washing and rinsing purposes. The composition is based on a modification of the injectable formula originally known as Hartmann's Solution.

Each 100 mL contains:
Sodium Chloride USP 0.6 g, Sodium Lactate 0.31 g, Potassium Chloride USP 0.03 g, Calcium Chloride Dihydrate USP 0.02 g, Water for Injection USP qs.

pH adjusted with Hydrochloric Acid NF
pH: 6.75 (6.0–7.5) Calculated Osmolarity: 275 mOsmol/liter

Concentration of Electrolytes (mEq/liter): Sodium 130, Potassium 4, Calcium 3, Chloride 110, Lactate (CH3CH(OH)COO^−) 28

The solution contains no bacteriostat, antimicrobial agent or added buffer (except for pH adjustment) and is intended only for use as a single-dose or short procedure irrigation. When smaller volumes are required the unused portions should be discarded. Lactated Ringer's Irrigation may be classified as a sterile irrigant, wash, rinse and pharmaceutical vehicle.

The formulas of the active ingredients are:

Ingredients | Molecular Formula | Molecular Weight
Sodium Chloride USP | NaCl | 58.44
Sodium Lactate | CH3CH(OH)COONa | 112.06
Potassium Chloride USP | KCl | 74.55
Calcium Chloride Dihydrate USP | CaCl2•2H2O | 147.01

The plastic container is a copolymer of ethylene and propylene formulated and developed for parenteral drugs. The copolymer contains no plasticizers and exhibits virtually no leachability. The plastic container is also virtually impermeable to vapor transmission and therefore, requires no overwrap to maintain the proper drug concentration. The safety of the plastic container has been confirmed by biological evaluation procedures. The material passes Class Vl testing as specified in the U.S. Pharmacopeia for Biological Tests — Plastic Containers. These tests have shown that the container is nontoxic and biologically inert.

Not made with natural rubber latex, PVC or DEHP.

CLINICAL PHARMACOLOGY

Lactated Ringer's Irrigation exerts a mechanical cleansing action for sterile irrigation of body cavities, tissues or wounds, indwelling urethral catheters and surgical drainage tubes, and for washing, rinsing or soaking surgical dressings, instruments and laboratory specimens. It also serves as a vehicle for drugs used for irrigation or other pharmaceutical preparations.

Lactated Ringer's Irrigation provides an isotonic irrigation with the same ionic constituents as Lactated Ringer's Injection, USP, a modification of Hartmann's Solution.Lactated Ringer's Irrigation is considered generally compatible with living tissues and organs.

Calcium chloride in water dissociates to provide calcium (Ca^++) and chloride (Cl^−) ions. They are normal constituents of the body fluids and are dependent on various physiologic mechanisms for maintenance of balance between intake and output. Approximately 80% of body calcium is excreted in the feces as insoluble salts; urinary excretion accounts for the remaining 20%.

Potassium chloride in water dissociates to provide potassium (K^+) and chloride (Cl^−) ions. Potassium is the chief cation of body cells (160 mEq/liter of intracellular water). It is found in low concentration in plasma and extracellular fluids (3.5 to 5 mEq/liter in a healthy adult). Potassium plays an important role in electrolyte balance.

Normally about 80 to 90% of the potassium intake is excreted in the urine; the remainder in the stools and to a small extent, in the perspiration. The kidney does not conserve potassium well so that during fasting or in patients on a potassium-free diet, potassium loss from the body continues resulting in potassium depletion.

Sodium chloride in water dissociates to provide sodium (Na^+) and chloride (Cl^−) ions. Sodium (Na^+) is the principal cation of the extracellular fluid and plays a large part in the therapy of fluid and electrolyte disturbances. Chloride (Cl^−) has an integral role in buffering action when oxygen and carbon dioxide exchange occurs in the red blood cells. The distribution and excretion of sodium (Na^+) and chloride (Cl^−) are largely under the control of the kidney which maintains a balance between intake and output.

Sodium lactate in water dissociates to provide sodium (Na^+) and lactate (C3H5O^−3) ions. The lactate anion provides an alkalizing effect resulting from simultaneous removal by the liver of lactate and hydrogen ions. In the liver, the lactate is metabolized to glycogen which is ultimately converted to carbon dioxide and water by oxidative metabolism.

The lactate anion acts as a source (alternate) of bicarbonate when normal production and utilization of lactic acid is not impaired as a result of disordered lactate metabolism. Since metabolic conversion is dependent on the integrity of cellular oxidative processes, lactate may be inadequate or ineffective as a source of bicarbonate in patients suffering from acidosis associated with shock or other disorders involving reduced perfusion of body tissues. When oxidative activity is intact, one to two hours time is required for metabolism of lactate.

Water is an essential constituent of all body tissues and accounts for approximately 70% of total body weight. Average normal adult daily requirement ranges from two to three liters (1 to 1.5 liters each for insensible water loss by perspiration and urine production).

Water balance is maintained by various regulatory mechanisms. Water distribution depends primarily on the concentration of electrolytes in the body compartments and sodium (Na^+) plays a major role in maintaining physiologic equilibrium.

INDICATIONS AND USAGE

Lactated Ringer's Irrigation is indicated for all general irrigation, washing and rinsing purposes which permit use of a sterile, nonpyrogenic electrolyte solution.

CONTRAINDICATIONS

NOT FOR INJECTION BY USUAL PARENTERAL ROUTES.

An electrolyte solution should not be used for irrigation during electrosurgical procedures.

WARNINGS

FOR IRRIGATION ONLY. NOT FOR INJECTION.

Irrigating fluids have been demonstrated to enter the systemic circulation in relatively large volumes; thus this irrigation must be regarded as a systemic drug. Absorption of large amounts can cause fluid and/or solute overloading resulting in dilution of serum electrolyte concentrations, overhydration, congested states or pulmonary edema.

The risk of dilutional states is inversely proportional to the electrolyte concentrations of administered parenteral solutions. The risk of solute overload causing congested states with peripheral and pulmonary edema is directly proportional to the electrolyte concentrations of such solutions.

Do not warm container over 150°F (66°C).

PRECAUTIONS

General

Do not use for irrigation that may result in absorption into the blood.

Caution should be observed when the solution is used for continuous irrigation or allowed to "dwell" inside body cavities because of possible absorption into the blood stream and the production of circulatory overload.

Aseptic technique is essential with the use of sterile solutions for irrigation of body cavities, wounds and urethral catheters or for wetting dressings that come in contact with body tissues.

When used as a "pour" irrigation, no part of the contents should be allowed to contact the surface below the outer protected thread area of the plastic irrigation container. When used for irrigation via irrigation equipment, the administration set should be attached promptly. Unused portions should be discarded and a fresh container of appropriate size used for the start-up of each cycle or repeat procedure. For repeated irrigations of urethral catheters, a separate container should be used for each patient

Use only if solution is clear and container and seal are intact.

Pregnancy:

Teratogenic Effects

Animal reproduction studies have not been conducted with Lactated Ringer’s Irrigation. It is also not known whether it can cause fetal harm when administered to a pregnant woman or can affect reproduction capacity. It should be given to a pregnant woman only if clearly needed.

Pediatric Use

The safety and effectiveness of Lactated Ringer's Irrigation have not been established. Its limited use in pediatric patients has been inadequate to fully define proper dosage and limitations for use.

ADVERSE REACTIONS

Possible adverse effects arising from the irrigation of body cavities, tissues, or indwelling catheters and tubes are usually avoidable when proper procedures are followed. Displaced catheters or drainage tubes can lead to irrigation or infiltration of unintended structures or cavities. Excessive volume or pressure during irrigation of closed cavities may cause undue distension or disruption of tissues. Accidental contamination from careless technique may transmit infection.

Should any adverse reaction occur, discontinue the irrigant, evaluate the patient, institute appropriate therapeutic countermeasures and save the remainder of the fluid for examination if deemed necessary.

OVERDOSAGE

In the event of overhydration or solute overload, re-evaluate the patient and institute appropriate corrective measures. See WARNINGS, PRECAUTIONS and ADVERSE REACTIONS.

DOSAGE AND ADMINISTRATION

The dose is dependent upon the capacity or surface area of the structure to be irrigated and the nature of the procedure. When used as a vehicle for other drugs, the manufacturer's recommendations should be followed.

Drug Interactions

Additives may be incompatible. Consult with pharmacist, if available. When introducing additives, use aseptic technique, mix thoroughly and do not store.

Parenteral drug products should be inspected visually for particulate matter and discoloration prior to administration, whenever solution container permits. See PRECAUTIONS.

HOW SUPPLIED

Lactated Ringer's Irrigation is supplied sterile and nonpyrogenic in PIC™ (Plastic Irrigation Container). The 1000 mL containers are packaged 16 per case.

NDC | Cat. No. | Size
Lactated Ringer's Irrigation
0264-2203-00 | R5410-01 | 1000 mL

STORAGE AND HANDLING

Exposure of pharmaceutical products to heat should be minimized. Avoid excessive heat. Protect from freezing. Store at 20°C to 25°C (68°F to 77°F); excursions permitted between 15°C to 30°C (59°F to 86°F). [See USP Controlled Room Temperature.] However, brief exposure up to 40°C does not adversely affect the product.

Do not warm above 150°F (66°C).

Revised: June 2023
PIC is a trademark of B. Braun Medical Inc.

Directions for Use of PIC™ (Plastic Irrigation Container)

Not for injection.

Aseptic technique is required.

1. Caution – Before use, perform the following checks:
  (a) Read the label. Ensure solution is the one ordered and is within the expiration date.
  (b) Invert container and inspect the solution in good light for cloudiness, haze, or particulate matter; check the container for leakage or damage. Any container which is suspect should not be used.
  Use only if solution is clear and container and seal are intact.
  Single-dose container. Discard unused portion.
2. Outer Closure Removal – Grasp the container with one hand and turn the breakaway ring counterclockwise with the other hand until slight resistance is felt. Then, twisting the container in the opposite direction, turn the breakaway ring sharply until the entire outer cap is loose and can be lifted off. (Figure 1)
3. Connect the administration set through the sterile set port according to set instructions (Figure 2) or remove screw cap and pour.
4. Do not warm above 150°F (66°C) to assure minimal bottle distortion. Keep bottles upright.

B. Braun Medical Inc.
Bethlehem, PA 18018-3524 USA
1-800-227-2862

PRINCIPAL DISPLAY PANEL - 1000 mL Label

Lactated Ringer's Irrigation

Isotonic Solution for Irrigation

REF R5410-01 | HK 22614
NDC 0264-2203-00

1000 mL
PIC™ Container

Rx only

Lot

Exp.

Each 100 mL contains:
Sodium Chloride USP 0.6 g
Sodium Lactate 0.31 g
Potassium Chloride USP 0.03 g
Calcium Chloride•2H2O USP 0.02 g
Water for Injection USP qs
pH adjusted with HCl NF

pH: 6.75 (6.0 – 7.5)
Calc. Osmolarity: 275 mOsmol/liter

Electrolytes (mEq/liter): Na^+ 130
K^+ 4 Ca^++ 3 Cl^− 110 Lactate 28

Sterile, nonpyrogenic. Single-dose container.

Discard unused portion.

Not for Injection. Use only if solution is clear and container and seal are intact.

Warning: Do not warm above 150°F (66°C).

Store at 20°C to 25°C (68°F to 77°F). [See USP Controlled Room Temperature.] Avoid excessive heat. Protect from freezing.
Dosage: See Prescribing Information

Rx only

Not made with natural rubber latex, PVC or DEHP.

B. Braun Medical Inc.
Bethlehem, PA 18018-3524 USA
1-800-227-2862

Y37-002-528 LD-781-1

Lactated Ringer's Irrigation